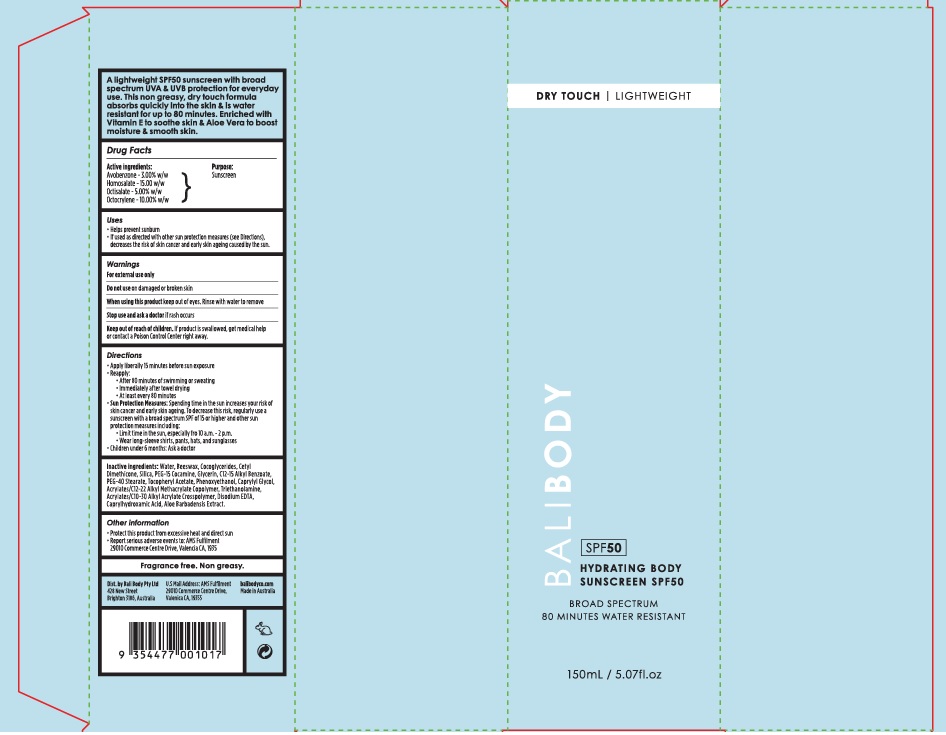 DRUG LABEL: Bali Body Hydrating Body Sunscreen SPF50
NDC: 70630-0025 | Form: LOTION
Manufacturer: Bali Body Pty Ltd
Category: otc | Type: HUMAN OTC DRUG LABEL
Date: 20241021

ACTIVE INGREDIENTS: OCTISALATE 50 mg/1 mL; OCTOCRYLENE 100 mg/1 mL; HOMOSALATE 150 mg/1 mL; AVOBENZONE 30 mg/1 mL
INACTIVE INGREDIENTS: SILICON DIOXIDE; WATER; ALKYL (C12-15) BENZOATE; CETYL DIMETHICONE 45; ALOE VERA WHOLE; YELLOW WAX; PEG-15 COCAMINE; CAPRYLYL GLYCOL; GLYCERIN; CARBOMER INTERPOLYMER TYPE A (55000 CPS); .ALPHA.-TOCOPHEROL ACETATE; COCO-GLYCERIDES; PEG-40 STEARATE; PHENOXYETHANOL; EDETATE DISODIUM ANHYDROUS; TROLAMINE; CAPRYLHYDROXAMIC ACID

Bali Body Hydrating Body Sunscreen SPF50

Active ingredients

Avobenzone - 3.00% w/w

Homosalate - 15.00% w/w

Octisalate - 5.00% w/w

Octocrylene - 10.00% w/w

Purpose

Sunscreen

Uses

- Helps prevent sunburn
- If used as directed with other sun protection measures (see Directions), decreases the risk of skin cancer and early skin ageing caused by the sun.

Warnings

For external use only

Do not use

on damaged or broken skin

When using this product

keep out of eyes. Rinse with water to remove

Stop use and ask a doctor

if rash occurs

Keep out of reach of children.

If product is swallowed, get medical help or contact a Poison Control Center right away.

Directions

- Apply liberally 15 minutes before sun exposure
- Reapply:
- After 80 minutes of swimming or sweating
- Immediately after towel drying
- At least every 80 minutes
- Sun Protection Measures: Spending time in the sun increases your risk of skin cancer and early skin ageing. To decrease this risk, regularly use a sunscreen with a broad spectrum SPF of 15 or higher and other sun protection measures including:
- Limit time in the sun, especially from 10 a.m. - 2 p.m.
- Wear long-sleeve shirts, pants, hats, and sunglasses
- Children under 6 months: Ask a doctor

Inactive ingredients

Water, Beeswax, Cocoglycerides, Cetyl Dimethicone, Silica, PEG-15 Cocamine, Glycerin, C12-15 Alkyl Benzoate, PEG-40 Stearate, Tocopheryl Acetate, Phenoxyethanol, Caprylyl Glycol, Acrylates/C12-22 Alkyl Methacrylate Copolymer, Triethanolamine, Acrylates/C10-30 Alkyl Acrylate Crosspolymer, Disodium EDTA, Caprylhydroxamic Acid, Aloe Barbadensis Extract.

Other information

- Protect this product from excessive heat and direct sun
- Report serious adverse events to: AMS Fulfilment 29010 Commerce Centre Drive, Valencia CA, 19355

Company Information

Dist. by Bali Body Pty Ltd

428 New Street

Brighton 3186, Australia

balibodyco.com